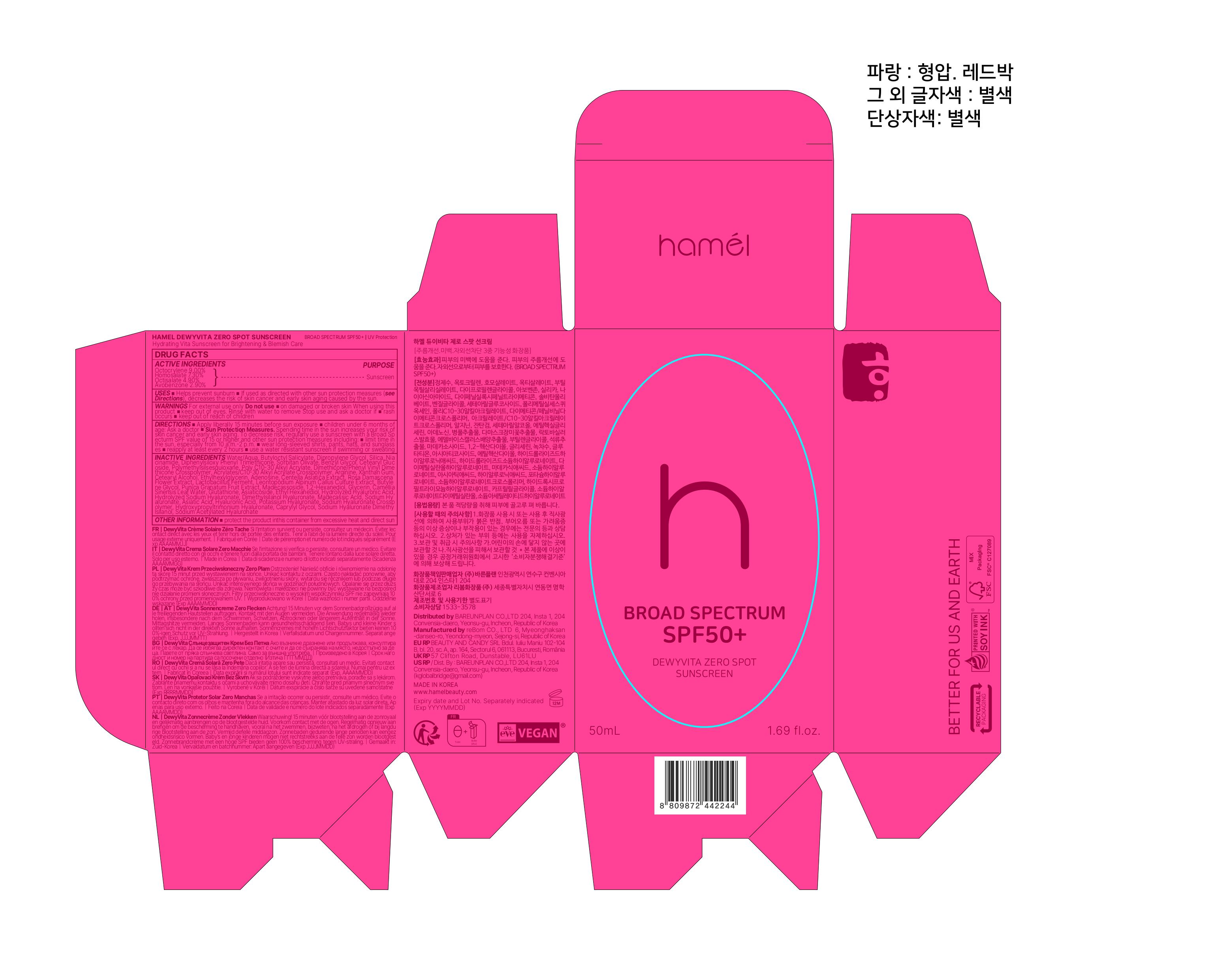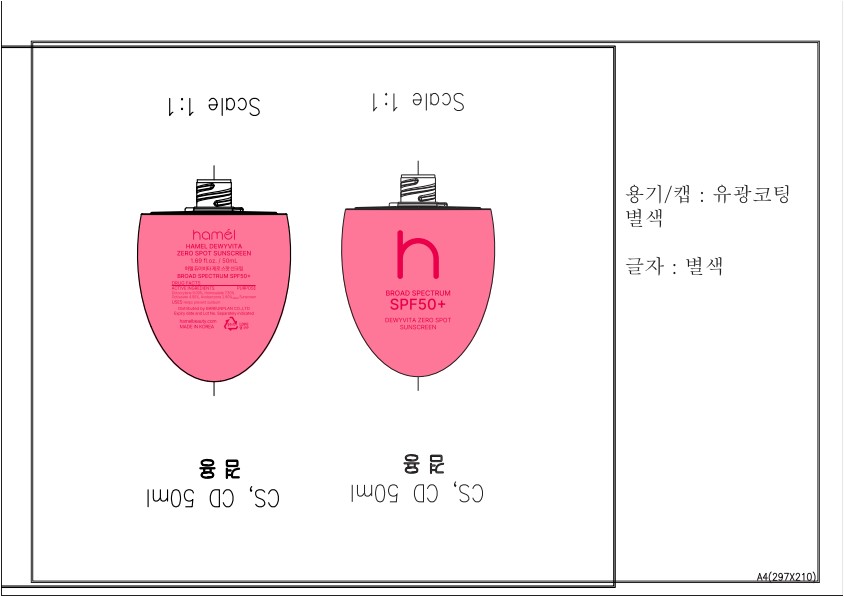 DRUG LABEL: DewyVita Zero Spot Sunscreen
NDC: 87350-100 | Form: CREAM
Manufacturer: BAREUNPLAN CO.,LTD.
Category: otc | Type: HUMAN OTC DRUG LABEL
Date: 20260121

ACTIVE INGREDIENTS: OCTISALATE 1.176 g/24 g; HOMOSALATE 1.752 g/24 g; AVOBENZONE 0.696 g/24 g; OCTOCRYLENE 2.16 g/24 g
INACTIVE INGREDIENTS: XANTHAN GUM; GLYCERIN; LEONTOPODIUM ALPINUM; BUTYLENE GLYCOL; BUTYLOCTYL SALICYLATE; SILICA; ETHYLHEXYLGLYCERIN; WATER; NIACINAMIDE; DIPHENYLSILOXY PHENYL TRIMETHICONE; ACRYLATES/C10-30 ALKYL ACRYLATE CROSSPOLYMER (60000 MPA.S); MADECASSOSIDE; CETEARYL GLUCOSIDE; BEHENYL ACRYLATE POLYMER; ARGININE; ADENOSINE; CAPRYLYL GLYCOL; SODIUM HYALURONATE; 1,2-HEXANEDIOL; SORBITAN OLIVATE; CENTELLA ASIATICA; GLUTATHIONE; ASIATICOSIDE; ETHYL HEXANEDIOL; HYALURONIC ACID; MADECASSIC ACID; BENZYL GLYCOL; DIMETHICONE/PHENYL VINYL DIMETHICONE CROSSPOLYMER; CETEARYL ALCOHOL; LIMOSILACTOBACILLUS FERMENTUM; PUNICA GRANATUM FRUIT JUICE; DIMETHYLSILANOL HYALURONATE; CAMELLIA SINENSIS LEAF; ASIATIC ACID; ROSA DAMASCENA FLOWER; DIPROPYLENE GLYCOL; POLYMETHYLSILSESQUIOXANE (11 MICRONS)

87350-100 DEWYVITA ZERO SPOT SUNSCREEN

ACTIVE INGREDIENT

Octocrylene 9.00%

Homosalate 7.30%

Octisalate 4.90%

Avobenzone 2.90%

PURPOSE

Sunscreen

INDICATIONS AND USAGE

■ Helps preven sunburn ■ If used as directed with other sun protection measures (see Directions), decreases the risk of skin cancer and early skin aging caused by the sun.

WARNINGS

For external use only.

Do not use ■ on damaged or broken skin.

When using this product ■ keep out of eyes. Rinse with water to remove.

Stop use and ask a doctor if ■ rash occurs.

■ keep out of reach of children.

DOSAGE AND ADMINISTRATION

■ Apply liberally 15 minutes before sun exposure ■ children under 6 months of age: Ask a doctor ■ Sun Protection Measures.Spending time in the sun increases your risk of skin cancer and early skin aging. To decrease risk, regularly use a sunscreen with a Broad Spectrum SPF value of 15 or higher and other sun protection measures including: ■ limit time in the sun, especially from 10 a.m.-2 p.m. ■ wear long-sleeved shirts, pants, hats, and sunglasses ■ reapply at least every 2 hours ■ use a water resistant sunscreen if swimming or sweating

INACTIVE INGREDIENT

Water/Aqua, Butyloctyl Salicylate, Dipropylene Glycol, Silica, Nia cinamide, Diphenylsiloxy Phenyl Trimethicone, Sorbitan Olivate, Benzyl Glycol, Cetearyl Glucoside, Polymethylsilsesquioxane, Poly C10-30 Alkyl Acrylate, Dimethicone/Phenyl Vinyl Dimethicone Crosspolymer, Acrylates/C10-30 Alkyl Acrylate Crosspolymer, Arginine, Xanthan Gum, Cetearyl Alcohol, Ethylhexylglycerin, Adenosine, Centella Asiatica Extract, Rosa Damascena Flower Extract, Lactobacillus Ferment, Leontopodium Alpinum Callus Culture Extract, Butylene Glycol, Punica Granatum Fruit Extract, Madecassoside, 1,2-Hexanediol, Glycerin, Camellia Sinensis Leaf Water, Glutathione, Asiaticoside, Ethyl Hexanediol, Hydrolyzed Hyaluronic Acid, Hydrolyzed Sodium Hyaluronate, Dimethylsilanol Hyaluronate, Madecassic Acid, Sodium Hyaluronate, Asiatic Acid, Hyaluronic Acid, Potassium Hyaluronate, Sodium Hyaluronate Crosspolymer, Hydroxypropyltrimonium Hyaluronate, Caprylyl Glycol, Sodium Hyaluronate DimethyIsilanol, Sodium Acetylated Hyaluronate

OTHER SAFETY INFORMATION

■ protect the product in this container from excessive heat and direct sun.